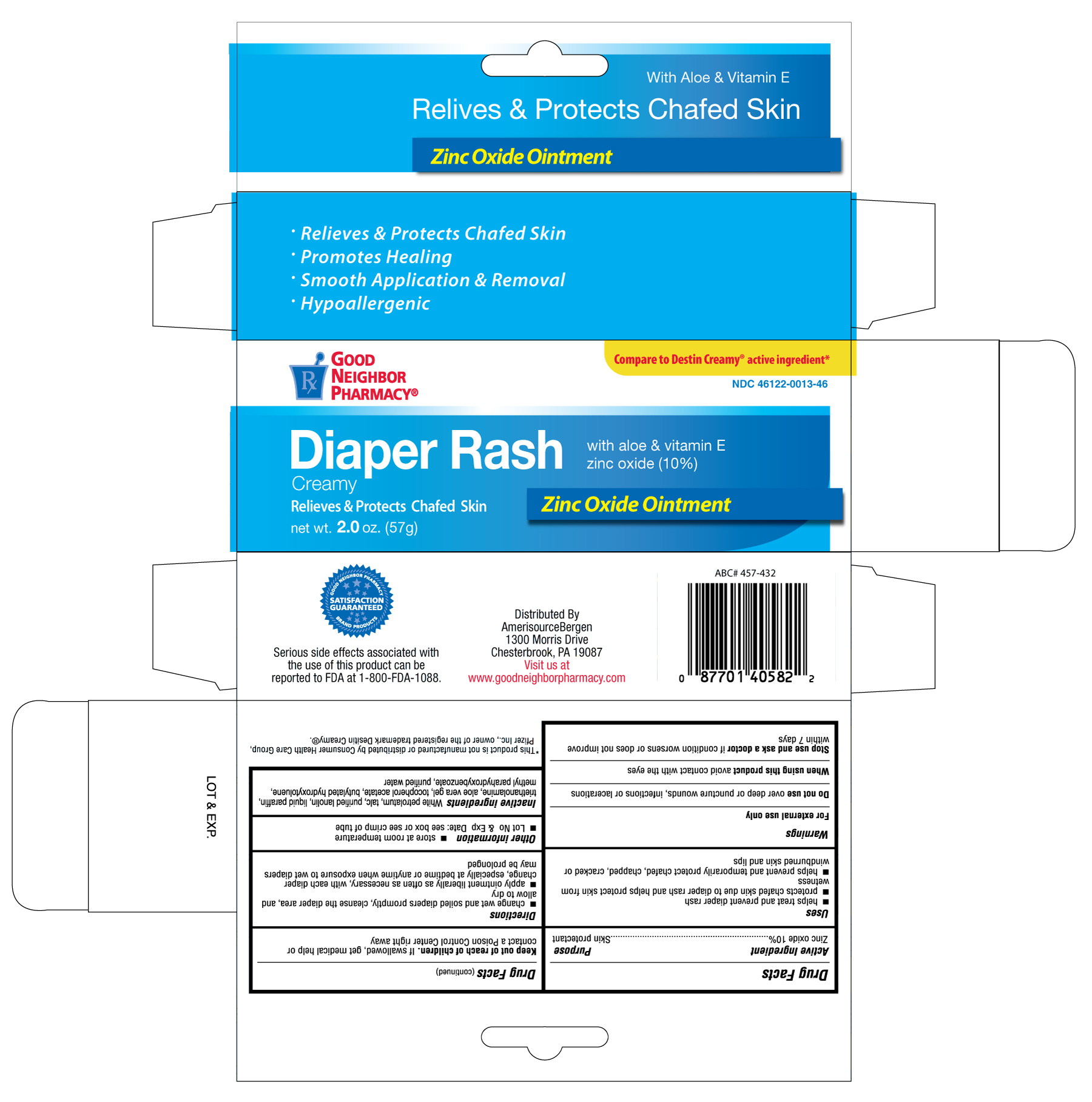 DRUG LABEL: GOOD NEIGHBOR PHARMACY DIAPER RASH CREAMY
NDC: 46122-013 | Form: OINTMENT
Manufacturer: AMERISOURCE BERGEN
Category: otc | Type: HUMAN OTC DRUG LABEL
Date: 20120501

ACTIVE INGREDIENTS: ZINC OXIDE 0.10 g/1 g
INACTIVE INGREDIENTS: PETROLATUM; TALC; LANOLIN; MINERAL OIL; TROLAMINE; BUTYLATED HYDROXYTOLUENE; WATER

Drug Facts

Active Ingredient Purpose

Zinc oxide 10% ........................................................................ Skin protectant

Uses

- helps treat and prevent diaper rash
- protects chafed skin due to diaper rash and helps protect skin from wetness
- helps prevent and temporarily protect chafed, chapped, cracked or windburned skin and lips

Warnings

For external use only

Do not use over deep or puncture wounds, infections or lacerations

When using this product avoid contact with the eyes

Stop use and ask a doctor if condition worsens or does not improve within 7 days

Keep out of reach of children. If swallowed, get medical help or contact a Poison Control Center right away

Directions

- change wet and soiled diapers promptly, cleanse the diaper area and allow to dry
- apply ointment liberally as often as necessary, with each diaper change, especially at bedtime or anytime when exposure to wet diapers may be prolonged

Other information

- store at room temperature
- Lot No and Exp. Date: see box or see crimp of tube

Inactive ingredients

White petrolatum, talc, purified lanolin, liquid paraffin, triethanolamine, aloe vera gel, tocopherol acetate, butylated hydroxyloluene, methyl parahydroxybenzoate, purified water

DOSAGE AND ADMINISTRATION

Distributed By

Amerisource Bergen

1300 Morris Drive

Chesterbrook, PA 19087

Visit us at www.goodneighborpharmacy.com

Made in Korea

PACKAGE LABEL

Enter section text here